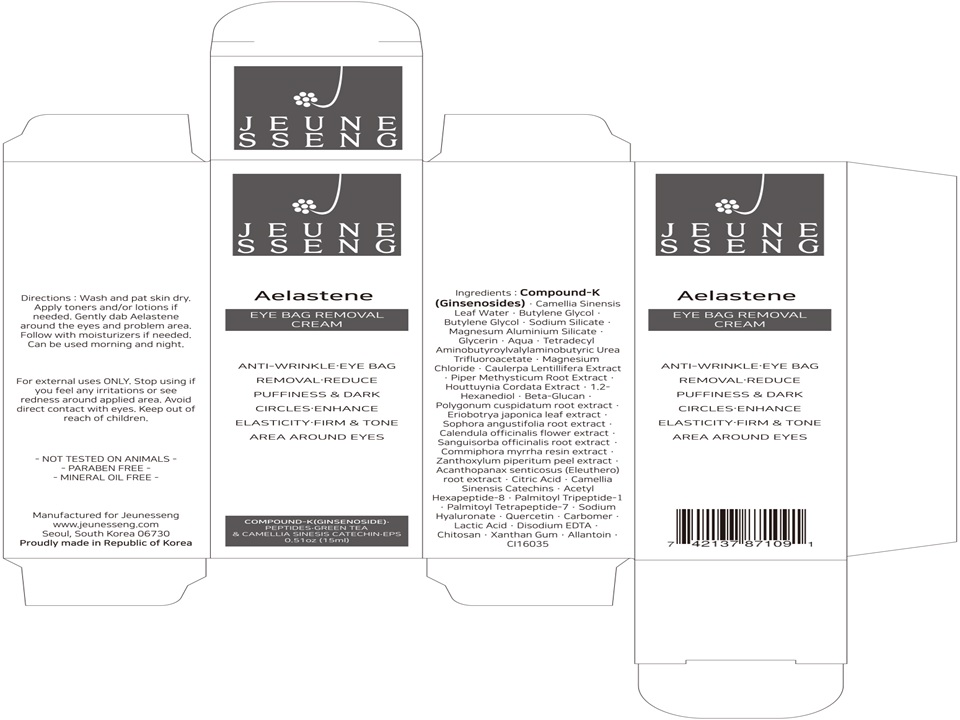 DRUG LABEL: JEUNESSENG EYE BAG REMOVAL
NDC: 71703-0001 | Form: CREAM
Manufacturer: Frontier EDU
Category: otc | Type: HUMAN OTC DRUG LABEL
Date: 20170829

ACTIVE INGREDIENTS: ADENOSINE 0.04 g/100 mL
INACTIVE INGREDIENTS: WATER; GLYCERIN

Drug Facts

ACTIVE INGREDIENT

ADENOSINE

INACTIVE INGREDIENT

Compound-K(Ginsenosides)
Aqua
Acetyl Hexapeptide-8
Butylene Glycol
Sodium Metasilicate
Camellia Sinensis Leaf Extract
Camellia Sinensis Catechins
Phenoxyethanol
Dipotassium Glycyrrhizate
Ethylhexylglycerin
Portulaca Oleracea Extract
Coptis Japonica Root Extract
Phellodendron Amurense Bark Extract
Astragalus Membranaceus Root Extract
Scutellaria Baicalensis Root Extract
Polygonatum Odoratum Extract
Ammonium Aacryloyldimethyl Taurate/VP copolymer
Sodium Polyacrylate
Macadamia Integrifolia Seed Oil
Cocos Nucifera (Coconut) Oil
Oryza Sativa (Rice) Bran Oil
Persea Gratissima (Avocado) Oil
Olus
Tocopherol
Glycerin
Palmitoyl Tripeptide-5
Lecithin
Lepidium Sativum Sprout Extract
Caprylic/Capric Triglyceride
Centella Asiatica Extract
Hydrogenated Lecithin
Cholesterol
Octyldodecanol
Polyglyceryl-10 Myristate
Phytosterols
Ligustrum Japonicum Fruit Extract
Pentylene Glycol
Sodium Phosphate
sh-Oligopeptide-1
CI 77492
Synthetic Fluorophlogopite
Disodium N-Stearoyl-L-glutamate
Aluminum Dimyristate
Xanthan Gum
Aluminum Hydroxide
CI 77491
Fragrance
CI 77499
1,2-Hexanediol
Alcohol

PURPOSE

- Anti-Wrinkle eye bag
- Removal eeduce
- Puffiness & Dark
- Circles-Enhance
- Elasticity-Firm & Tone
- Area around eyes

keep out of reach of the children

INDICATIONS AND USAGE

- Wash and pat skin dry.
- Apply toners and/or lotions if needed.
- Gently dab Aelastene around the eyes and problem area.
- Follow with moisturizers if needed.
- Can be used morning and night.

WARNINGS

- For external uses ONLY.
- Stop using if you feel any irritations or see redness around applied area.
- Avoid direct contact with eyes.
- Keep out of reach of children.

DOSAGE AND ADMINISTRATION

for external use only